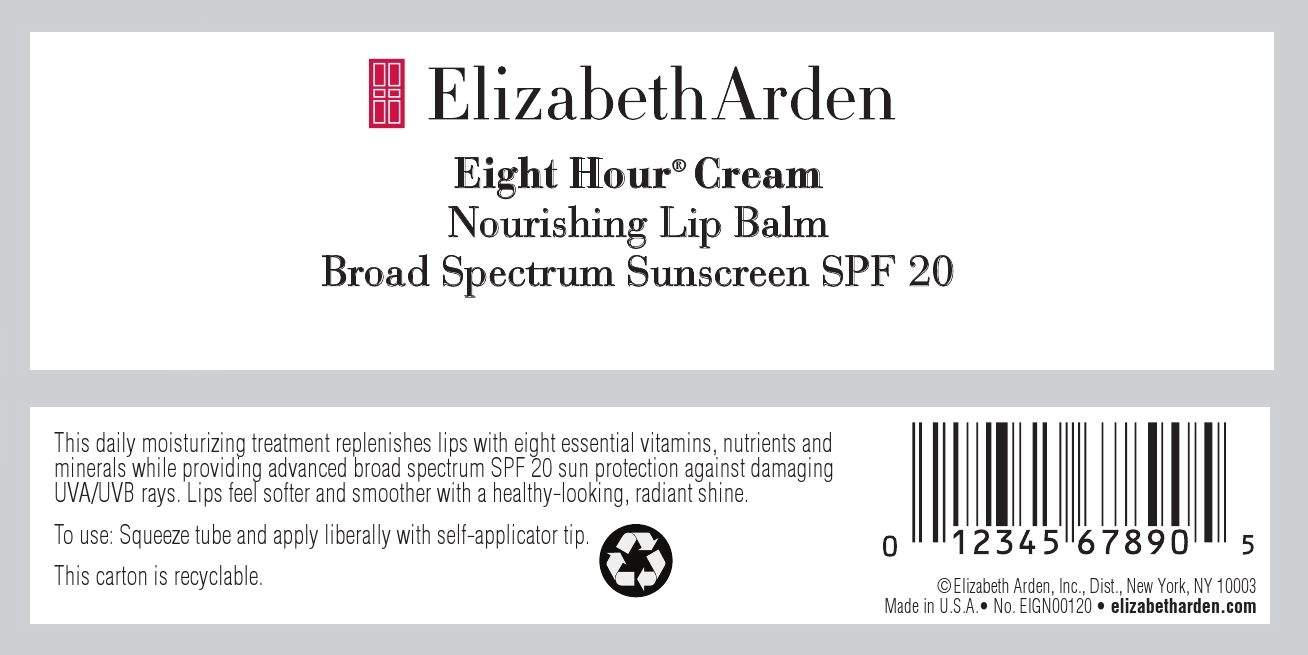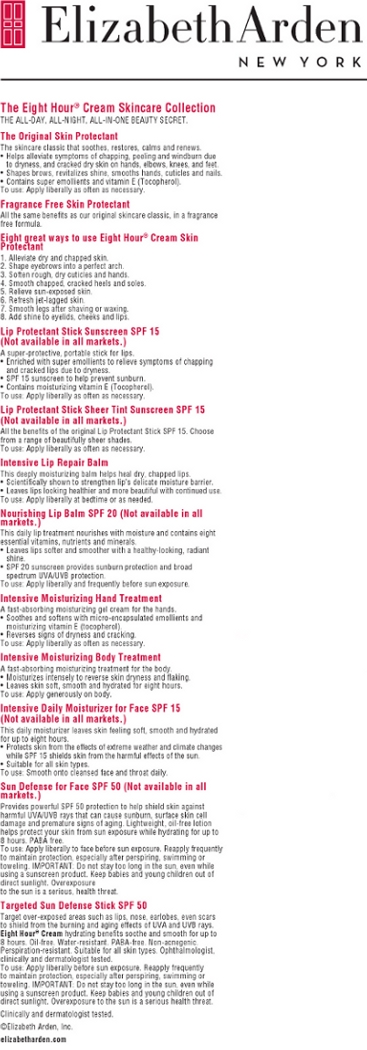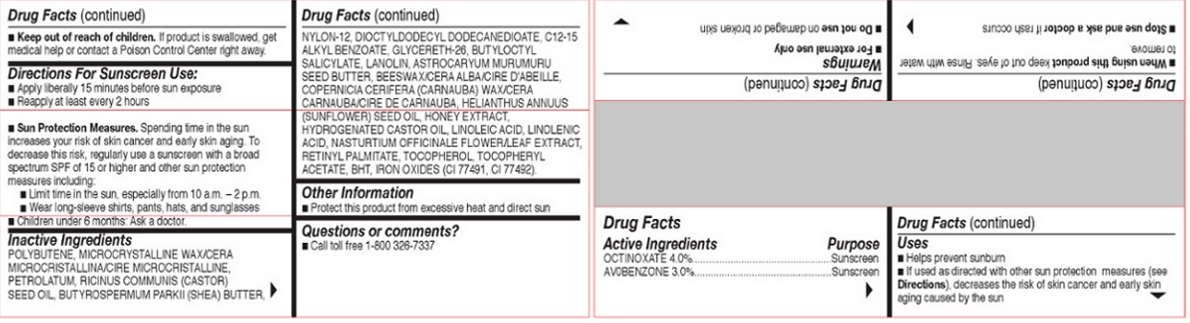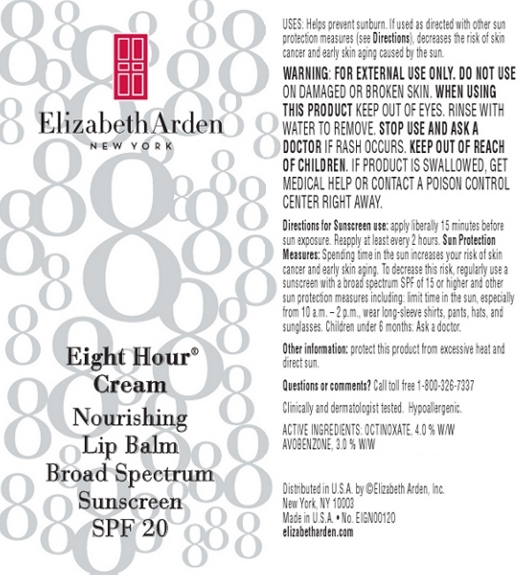 DRUG LABEL: Eight Hour Cream Nourishing Lip Balm SPF 20
NDC: 67938-1111 | Form: SALVE
Manufacturer: Elizabeth Arden, Inc
Category: otc | Type: HUMAN OTC DRUG LABEL
Date: 20130502

ACTIVE INGREDIENTS: OCTINOXATE 0.568 g/14.2 g; AVOBENZONE 0.426 g/14.2 g
INACTIVE INGREDIENTS: POLYBUTENE (1400 MW); MICROCRYSTALLINE WAX; PETROLATUM; NYLON-12; DIOCTYLDODECYL DODECANEDIOATE; GLYCERETH-26; BUTYLOCTYL SALICYLATE; LANOLIN; ASTROCARYUM MURUMURU SEED BUTTER; HYDROGENATED CASTOR OIL; LINOLEIC ACID; LINOLENIC ACID; TOCOPHEROL

197107

DESCRIPTION

This daily moisturizing treatment replenishes lips with eight essential vitamins, nutrients and

minerals while providing advanced broad spectrum SPF 20 sun protection against damaging

UVA/UVB rays.

INDICATIONS AND USAGE

To use: Squeeze tube and apply liberally with self-applicator tip.

WARNINGS

WARNING

:

FOR EXTERNAL USE ONLY. DO NOT USE

ON DAMAGED OR BROKEN SKIN. WHEN USING

THIS PRODUCT KEEP OUT OF EYES. RINSE WITH

WATER TO REMOVE. STOP USE AND ASK A

DOCTOR IF RASH OCCURS. KEEP OUT OF REACH

OF CHILDREN. IF PRODUCT IS SWALLOWED, GET

MEDICAL HELP OR CONTACT A POISON CONTROL

CENTER RIGHT AWAY.

OTC - ACTIVE INGREDIENT

ACTIVE INGREDIENTS: OCTINOXATE, 4.0 % W/W

AVOBENZONE, 3.0 % W/W

INACTIVE INGREDIENT

Inactive Ingredients

POLYBUTENE, MICROCRYSTALLINE WAX/CERA

MICROCRISTALLINA/CIRE MICROCRISTALLINE,

PETROLATUM, RICINUS COMMUNIS (CASTOR)

SEED OIL, BUTYROSPERMUM PARKII (SHEA) BUTTER,

NYLON-12, DIOCTYLDODECYL DODECANEDIOATE, C12-15

ALKYL BENZOATE, GLYCERETH-26, BUTYLOCTYL

SALICYLATE, LANOLIN, ASTROCARYUM MURUMURU

SEED BUTTER, BEESWAX/CERA ALBA/CIRE D'ABEILLE,

COPERNICIA CERIFERA (CARNAUBA) WAX/CERA

CARNAUBA/CIRE DE CARNAUBA, HELIANTHUS ANNUUS

(SUNFLOWER) SEED OIL, HONEY EXTRACT,

HYDROGENATED CASTOR OIL, LINOLEIC ACID, LINOLENIC

ACID, NASTURTIUM OFFICINALE FLOWER/LEAF EXTRACT,

RETINYL PALMITATE, TOCOPHEROL, TOCOPHERYL

ACETATE, BHT, IRON OXIDES (CI 77491, CI 77492).

DOSAGE & ADMINISTRATION

apply liberally

OTC - KEEP OUT OF REACH OF CHILDREN

KEEP OUT OF REACH OF CHILDREN.

OTC - PURPOSE

Provides SPF 20 sun protection.

OTC - WHEN USING

KEEP OUT OF EYES.